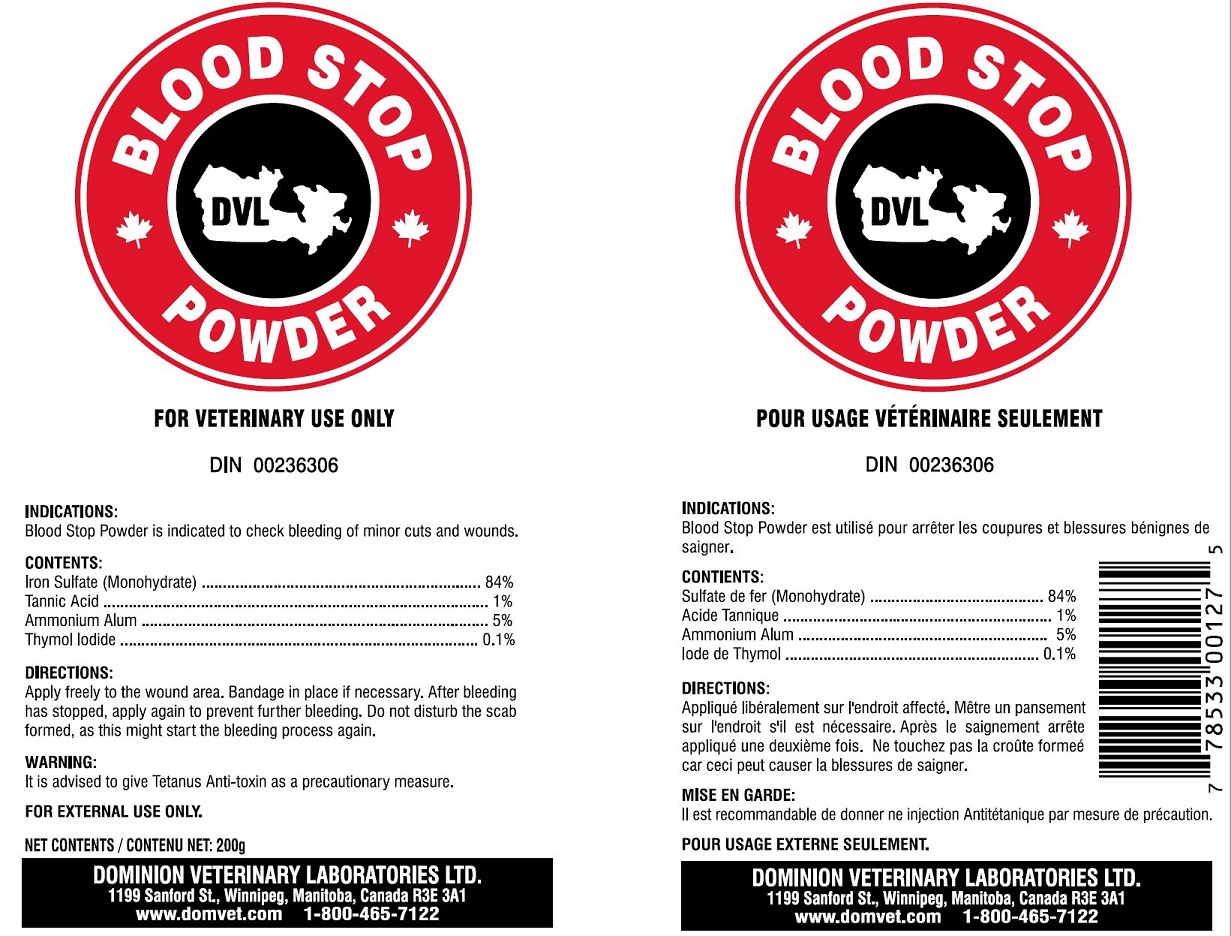 DRUG LABEL: BLOOD STOP
NDC: 64120-104 | Form: POWDER
Manufacturer: DOMINION VETERINARY LABORATORIES LTD.
Category: animal | Type: OTC ANIMAL DRUG LABEL
Date: 20211110

ACTIVE INGREDIENTS: FERROUS SULFATE ANHYDROUS 84 g/100 g
INACTIVE INGREDIENTS: TANNIC ACID; AMMONIUM ALUM; THYMOL IODIDE

DOMINION VETERINARY LABORATORIES - BLOOD STOP POWDER

INDICATIONS:

BLOOD STOP POWDER IS INDICATED TO CHECK BLEEDING OF MINOR CUTS AND WOUNDS.